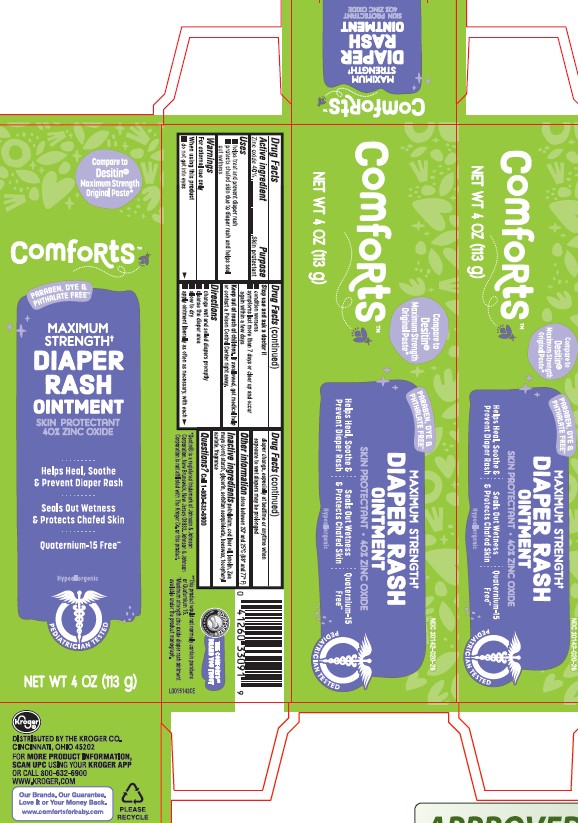 DRUG LABEL: Diaper Rash
NDC: 30142-020 | Form: PASTE
Manufacturer: The Kroger Co.
Category: otc | Type: HUMAN OTC DRUG LABEL
Date: 20260227

ACTIVE INGREDIENTS: ZINC OXIDE 400 mg/1 g
INACTIVE INGREDIENTS: PETROLATUM; COD LIVER OIL; LANOLIN; STARCH, CORN; GLYCERIN; SORBITAN SESQUIOLEATE; YELLOW WAX; .ALPHA.-TOCOPHEROL ACETATE

Comforts_Kroger 020.002/020AC-AD
Diaper Rash Ointment 40% Zinc Oxide

Active ingredient

Zinc oxide 40%

Purpose

Skin protectant

Uses

• helps treat and prevent diaper rash
• protects chafed skin due to the diaper rash and helps seal out wetness

Warnings

For external use only

When using this product

- do not get into eyes

Stop use and ask a doctor if

- condition worsens
- symptoms last more than 7 days or clear up and occur again within a few days

Keep out of reach of children.

If swallowed, get medical help or contact a Poison Control Center right away.

Directions

- change wet and soiled diapers promptly
- cleanse the diaper area
- allow to dry
- apply ointment liberally as often as necessary, with each diaper change, especially at bedtime or anytime when exposure to wet diapers may be prolonged

Other information

store between 20⁰ and 25⁰C (68⁰ and 77⁰F)

Inactive ingredients

petrolatum, cod liver oil, lanolin, Zea mays (corn) starch, glycerin, sorbitan sesquioleate, beeswax, tocoperyl acetate, fragrance

Questions?

Call 1-800-632-6900

Disclaimers

*Destin®is a registered trademark of Johnson & Johnson Corporation, New Brunswick, New Jersey 08933.

Johnson & Johnson Corporation is not affiliated with The Kroger Co. or this product.

The Comforts Brand You Trust™

**This product would not normally contain parabens or Quaternium 15.

†Maximum strength zinc oxide diaper rash ointment available under the product monograph.

Adverse event

DISTRIBUTED BY THE KROGER CO.

CINCINNATI, OHIO 45202

FOR MORE PRODUCT INFORMATION,

SCAN UPC USING YOUR KROGER APP

OR CALL 800-632-6900

WWW.KROGER.COM

Our Brands, Our Guarantee.

Love It or Your Money Back.

www.comfortsforbaby.com

Please Recycle

Principal display panel

NDC 30142-020-26

Compare to Desitin®Maximum Strength Original Paste*

COMFORTS™

Paraben, Dye & Phthalate Free**

MAXIMUM STRENGTH†

DIAPER RASH OINTMENT

Skin Protectant

40% ZINC OXIDE

Helps Heal, Soothe & Prevent Diaper Rash

Seals Out Wetness & Protects Chafed SKin

Quaternium 15 Free**

Hypoallergenic

Pediatrician Tested

NET WT 4 OZ (113 g)